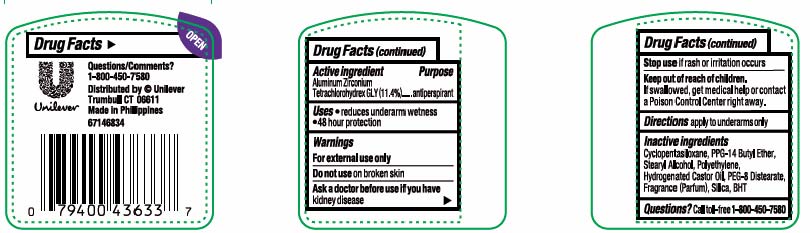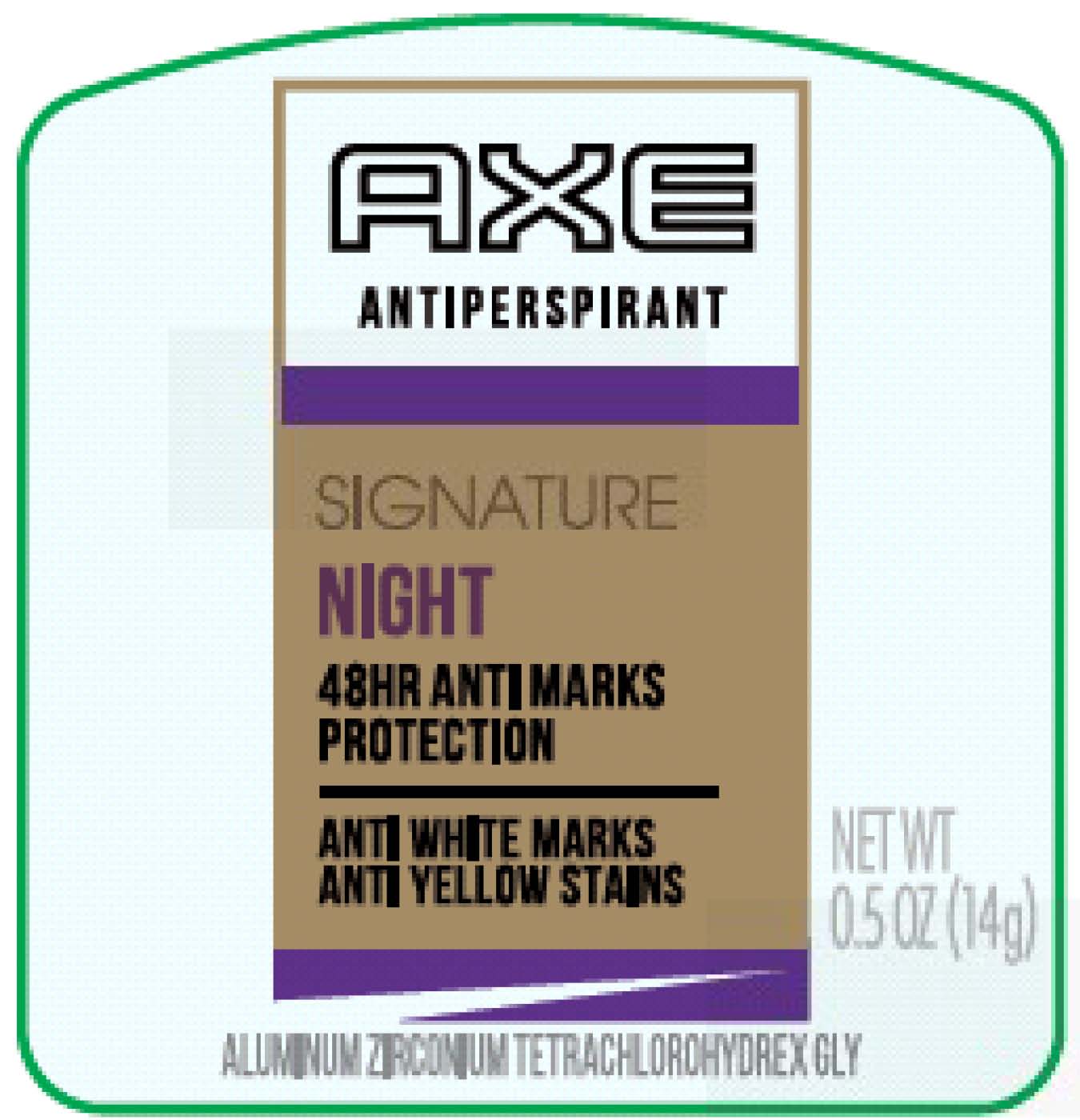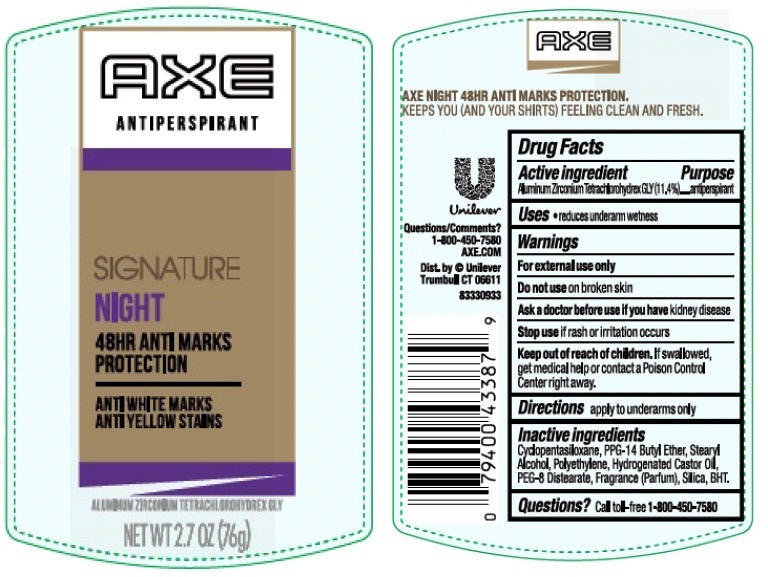 DRUG LABEL: Axe
NDC: 64942-1474 | Form: STICK
Manufacturer: Conopco, Inc. d/b/a/ Unilever
Category: otc | Type: HUMAN OTC DRUG LABEL
Date: 20241024

ACTIVE INGREDIENTS: ALUMINUM ZIRCONIUM TETRACHLOROHYDREX GLY 11.4 g/100 g
INACTIVE INGREDIENTS: CYCLOMETHICONE 5; PPG-14 BUTYL ETHER; STEARYL ALCOHOL; HIGH DENSITY POLYETHYLENE; HYDROGENATED CASTOR OIL; PEG-8 DISTEARATE; SILICON DIOXIDE; BUTYLATED HYDROXYTOLUENE

Axe - Signature Night Antiperspirant

Active ingredient

Aluminum Zirconium Tetrachlorohydrex GLY(11.4%)

Purpose

antiperspirant

Uses

• reduces underarm wetness

Warnings

For external use only
Do not use on broken skin
Ask a doctor before use if you have kidney disease
Stop use if rash or irritation occurs

Keep out of reach of children. If swallowed, get medical help or contact a Poison Control Center right away.

Directions

apply to underarms only

Inactive ingredients

Cyclopentasiloxane, PPG-14 Butyl Ether, Stearyl Alcohol, Polyethylene, Hydrogenated Castor Oil, PEG-8 Distearate, Fragrance (Parfum), Silica, BHT.

Questions?

Call toll-free 1-800-450-7580

48 HR ANTI MARKS PROTECTION
ANTI WHITE MARKS
ANTI YELLOW STAINS
AXE NIGHT 48HR ANTI MARKS PROTECTION.
KEEPS YOU (AND YOUR SHIRTS) FEELING CLEAN AND FRESH.